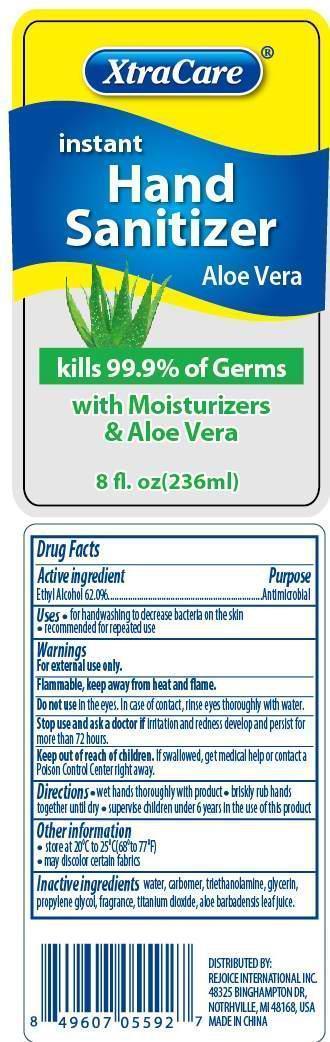 DRUG LABEL: Instant Hand Sanitizer Aloe Vera
NDC: 57337-012 | Form: GEL
Manufacturer: Rejoice International, Inc.
Category: otc | Type: HUMAN OTC DRUG LABEL
Date: 20240228

ACTIVE INGREDIENTS: ALCOHOL 146 mL/236 mL
INACTIVE INGREDIENTS: TROLAMINE; WATER; GLYCERIN; PROPYLENE GLYCOL; TITANIUM DIOXIDE; ALOE VERA LEAF; CARBOMER HOMOPOLYMER TYPE B

Instant Hand Sanitizer Aloe Vera

ACTIVE INGREDIENT

Ethyl Alcohol 62.0% ..................... Antimicrobial

PURPOSE

XtraCare Instant Hand Sanitizer Aloe Vera

kills 99.9% of germs

with Moisturizers & Aloe Vera

Keep out of reach of children. If swallowed, get medical help or contact a Poison Control Center right away.

INDICATIONS AND USAGE

- for handwashing to decrease bacteria on the skin
- recommended for repeated use

WARNINGS

For external use only.

Flammable, keep away from heat and flame.

Do not use in the eyes. In case of contact, rinse eyes thoroughly with water.

Stop use and ask a doctor if irritation and redness develop and persist for more than 72 hours.

Directions

- wet hands thoroughly with product
- briskly rub hands together until dry
- supervise children under 6 years in the use of this product

INACTIVE INGREDIENT

water, carbomer, triethanolamine, glycerin, propylene glycol, fragrance, titanium dioxide, aloe barbadensis leaf juice.

OTHER SAFETY INFORMATION

- store at 20oC to 25oC (68o to 77oF)
- may discolor certain fabrics